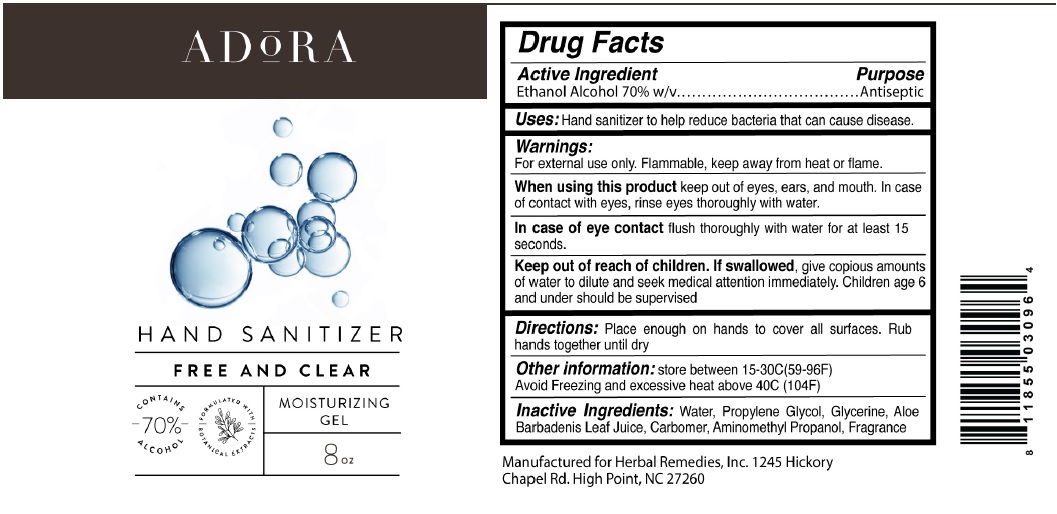 DRUG LABEL: Adora
NDC: 76842-700 | Form: GEL
Manufacturer: Adora
Category: otc | Type: HUMAN OTC DRUG LABEL
Date: 20200520

ACTIVE INGREDIENTS: ALCOHOL 70 mL/100 mL
INACTIVE INGREDIENTS: WATER; PROPYLENE GLYCOL; GLYCERIN; ALOE VERA LEAF; CARBOMER HOMOPOLYMER, UNSPECIFIED TYPE; AMINOMETHYLPROPANOL

ADORA HAND SANITIZER

Active Ingredient

Ethanol Alcohol 70% w/v

Purpose

Antiseptic

INDICATIONS AND USAGE

Uses: Hand sanitizer to help reduce bacteria that can cause disease.

Warnings:

For external use only. Flammable, Keep away from heat or flame.

When using this product keep out of eyes, ears, and mouth. In case of contact with eyes, rinse eyes thoroughly with water.

In case of eye contact flush thoroughly with water for at least 15 seconds.

Keep out of reach of children. If swallowed, give copious amounts of water to dilute and seek medical attention immediately. Children age 6 and under should be supervised

DOSAGE AND ADMINISTRATION

Directions: Place enough on hands to cover all surfaces. Rub hands together until dry

Other Information: store between 15-30C (59-96F)
Avoid freezing and excessive heat above 40C (104F)

INACTIVE INGREDIENT

Inactive Ingredients: Water, Propylene Glycol, Glycerine, Aloe Barbadensis Leaf Juice, Carbomer, Aminomethyl Propanol, Fragrance

FREE AND CLEAR

MOISTURIZING GEL

CONTAINS 70% ALCOHOL FORMULATED WITH BOTANICAL EXTRACTS

Manufactured for Herbal Remedies, Inc. 1245 Hickory

Chapel Rd. High Point, NC 27260